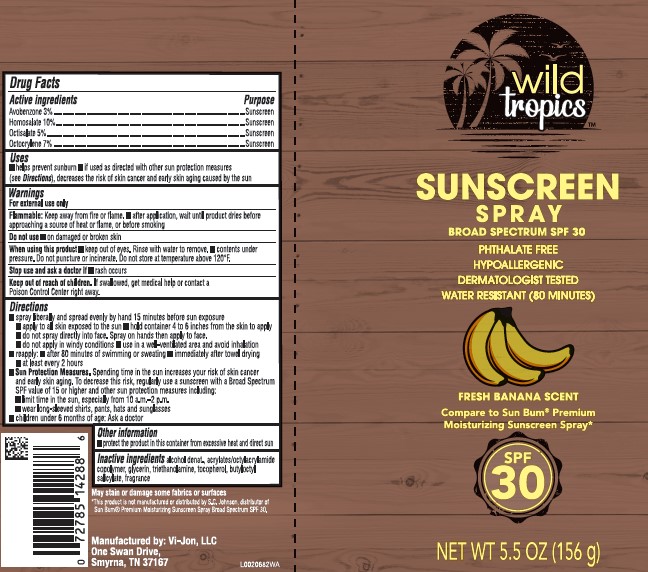 DRUG LABEL: Sunscreen SPF 30
NDC: 11344-109 | Form: SPRAY
Manufacturer: Consumer Product Partners, LLC
Category: otc | Type: HUMAN OTC DRUG LABEL
Date: 20250625

ACTIVE INGREDIENTS: HOMOSALATE 100 mg/1 g; OCTISALATE 50 mg/1 g; OCTOCRYLENE 70 mg/1 g; AVOBENZONE 30 mg/1 g
INACTIVE INGREDIENTS: ALCOHOL; ACRYLIC ACID/ISOPHORONE DIISOCYANATE/PEG-27 COPOLYMER; GLYCERIN; TROLAMINE; TOCOPHEROL; BUTYLOCTYL SALICYLATE

Wild Tropics 109.000/109AA
Sunscreen Spray SPF 30

Active ingredients

Avobenzone 3%

Homosalate 10%

Octisalate 5%

Octocrylene 7%

Purpose

Sunscreen

Uses

- helps prevent sunburn
- if used as directed with other sun protection measures (see Directions), decreases the risk of skin cancer and early skin aging caused by the sun

Warnings

For external use only

- Flammable: Keep away from fire or flame.
- after application, wait until product dries before approaching a source of heat or flame, or before smoking

Do not use

- on damaged or broken skin

When using this product

- keep out of eyes. Rinse with water to remove.
- contents under pressure. Do not puncture or incinerate. Do not store at temperature above 120ºF.

Stop use and ask a doctor if

- rash occurs

Keep out of reach of children.

If swallowed, get medical help or contact a Poison Control Center right away.

Directions

- spray liberally and spread evenly by hand 15 minutes before sun exposure
- apply to all skin exposed to the sun
- hold container 4 to 6 inches from the skin to apply
- do not apply in windy conditions
- use in a well-ventilated area and avoid inhalation
- reapply:
- after 80 minutes of swimming or sweating
- immediately after towel drying
- at least every 2 hours
- Sun Protection Measures. Spending time in the sun increases your risk of skin cancer and early skin aging. To decrease this risk, regularly use a sunscreen with a Broad Spectrum SPF value of 15 or higher and other sun protection measures including:
- limit time in the sun, especially from 10 a.m. – 2 p.m.
- wear long-sleeved shirts, pants, hats and sunglasses
- children under 6 months of age: Ask a doctor

Other information

- protect the product in this container from excessive heat and direct sun

Inactive ingredients

alcohol denat., acrylates/octylacrylamide copolymer, glycerin, triethanolamine, tocopherol, butyloctyl salicylate, fragrance

Disclaimer

May stain or damage some fabrics or surfaces

*This product is not manufactured or distributed by S.C. Johnson, distributor of Sun Bum® Premium Moisturizing Sunscreen Spray Broad Spectrum SPF 30.

Adverse reaction

Manufactured by: Vi-Jon, LLC

One Swan Drive

Smyrna, TN 37167

Principle display panel

Wild Tropics™

Sunscreen Spray

BROAD SPECTRUM SPF 30

Phthalate free

Hypoallergenic

Dermatologist tested

Water resistant (80 minutes)

Fresh Banana Scent

Compare to Sun Bum® Premium Moisturizing Sunscreen Spray*

SPF 30

NET WT 5.5 OZ (156 g)